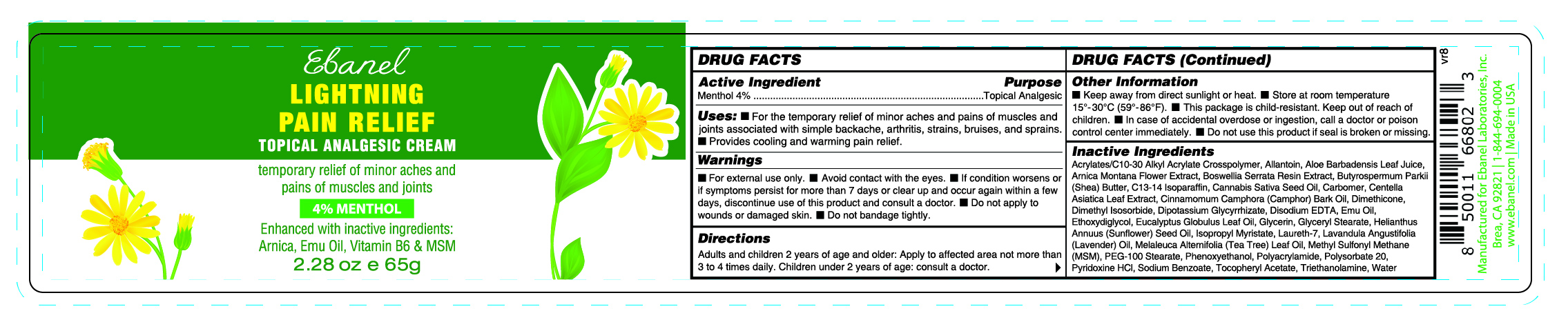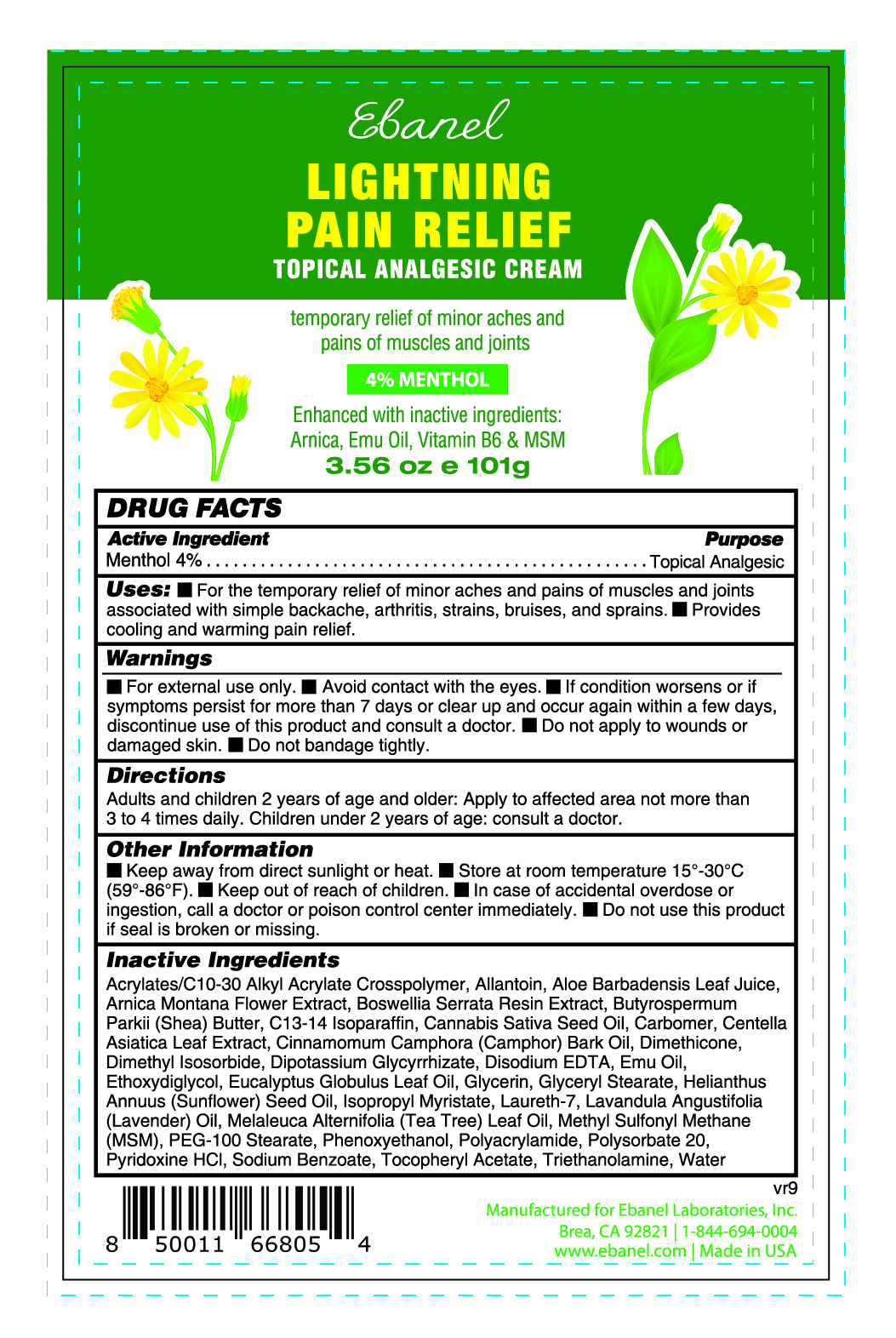 DRUG LABEL: Lightning Pain Relief
NDC: 72654-013 | Form: CREAM
Manufacturer: Ebanel Laboratories, Inc
Category: otc | Type: HUMAN OTC DRUG LABEL
Date: 20250606

ACTIVE INGREDIENTS: MENTHOL 40 mg/1 g
INACTIVE INGREDIENTS: CARBOMER; CANNABIS SATIVA SEED OIL; MELALEUCA ALTERNIFOLIA (TEA TREE) LEAF OIL; DIMETHYL SULFONE; PYRIDOXINE HCL; ALLANTOIN; ALOE BARBADENSIS LEAF JUICE; ARNICA MONTANA FLOWER; BUTYROSPERMUM PARKII (SHEA) BUTTER; C13-14 ISOPARAFFIN; CINNAMOMUM CAMPHORA (CAMPHOR) BARK OIL; DIMETHYL ISOSORBIDE; ETHOXYDIGLYCOL; GLYCERIN; GLYCERYL STEARATE; ISOPROPYL MYRISTATE; .ALPHA.-TOCOPHEROL ACETATE, D-; TRIETHANOLAMINE; WATER; BOSWELLIA SERRATA RESIN OIL; CENTELLA ASIATICA LEAF; DIPOTASSIUM GLYCYRRHIZATE; EMU OIL; HELIANTHUS ANNUUS (SUNFLOWER) SEED OIL; LAURETH-7; LAVANDULA ANGUSTIFOLIA (LAVENDER) OIL; PHENOXYETHANOL; POLYSORBATE 20; SODIUM BENZOATE; ACRYLATES/C10-30 ALKYL ACRYLATE CROSSPOLYMER (60000 MPA.S); DIMETHICONE; DISODIUM EDTA-COPPER; EUCALYPTUS GLOBULUS LEAF OIL; PEG-100 STEARATE; POLYACRYLAMIDE (10000 MW)

Active Ingredient

Menthol 4%

Active Ingredient Purpose

Menthol 4% Topical Analgesic

Directions

Adults and children 2 years of age and older: Apply to affected area not more than 3 to 4 times daily. Children under 2 years of age: consult a doctor.

Warnings

■ For external use only.

■ Avoid contact with the eyes.

■ If condition worsens or if symptoms persist for more than 7 days or clear up and occur again within a few days, discontinue use of this product and consult a doctor.

■ Do not apply to wounds or damaged skin.

■ Do not bandage tightly.

Uses

■ For the temporary relief of minor aches and pains of muscles and joints associated with simple backache, arthritis, strains, bruises, and sprains. ■ Provides cooling and warming pain relief.

Other Information

■ Keep away from direct sunlight or heat.

■ Store at room temperature 15°-30°C (59°-86°F).

■ This package is child-resistant. Keep out of reach of children.

■ In case of accidental overdose or ingestion, call a doctor or poison control center immediately.

■ Do not use this product if seal is broken or missing.

Inactive Ingredients

Acrylates/C10-30 Alkyl Acrylate Crosspolymer, Allantoin, Aloe Barbadensis Leaf Juice, Arnica Montana Flower Extract, Boswellia Serrata Resin Extract, Butyrospermum Parkii (Shea) Butter, C13-14 Isoparaffin, Cannabis Sativa Seed Oil, Carbomer, Centella Asiatica Leaf Extract, Cinnamomum Camphora (Camphor) Bark Oil, Dimethicone, Dimethyl Isosorbide, Dipotassium Glycyrrhizate, Disodium EDTA, Emu Oil, Ethoxydiglycol, Eucalyptus Globulus Leaf Oil, Glycerin, Glyceryl Stearate, Helianthus Annuus (Sunflower) Seed Oil, Isopropyl Myristate, Laureth-7, Lavandula Angustifolia (Lavender) Oil, Melaleuca Alternifolia (Tea Tree) Leaf Oil, Methyl Sulfonyl Methane (MSM), PEG-100 Stearate, Phenoxyethanol, Polyacrylamide, Polysorbate 20, Pyridoxine HCl, Sodium Benzoate, Tocopheryl Acetate, Triethanolamine, Water